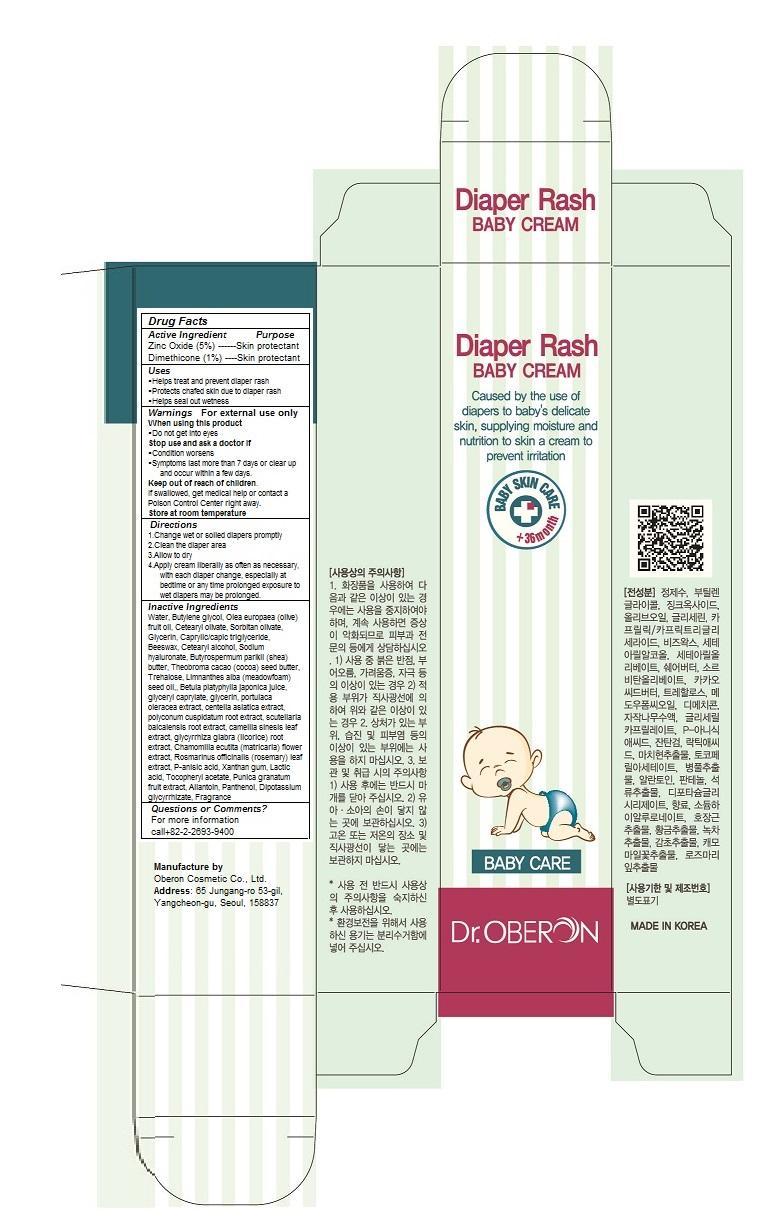 DRUG LABEL: Dr. Oberon Diaper Rash Baby Cream
NDC: 52891-104 | Form: CREAM
Manufacturer: Oberon Cosmetic Co., Ltd.
Category: otc | Type: HUMAN OTC DRUG LABEL
Date: 20140626

ACTIVE INGREDIENTS: ZINC OXIDE 0.75 g/15 g; DIMETHICONE 0.15 g/15 g
INACTIVE INGREDIENTS: Water; Butylene glycol; OLEA EUROPAEA FRUIT VOLATILE OIL; Cetearyl olivate; Sorbitan olivate; CAPRYLIC/CAPRIC/LAURIC TRIGLYCERIDE; YELLOW WAX; PEG-9 DIGLYCIDYL ETHER/SODIUM HYALURONATE CROSSPOLYMER; SHEA BUTTER; THEOBROMA CACAO WHOLE; Trehalose; LIMNANTHES ALBA WHOLE; BETULA PLATYPHYLLA VAR. JAPONICA RESIN; glyceryl caprylate; glycerin; PORTULACA OLERACEA WHOLE; CENTELLA ASIATICA; POLYGONUM CUSPIDATUM ROOT; SCUTELLARIA BAICALENSIS ROOT; CAMELLIA SINENSIS WHOLE; GLYCYRRHIZA GLABRA; MATRICARIA CHAMOMILLA FLOWERING TOP OIL; ROSMARINUS OFFICINALIS WHOLE; P-ANISIC ACID; XANTHAN GUM; LACTIC ACID; .ALPHA.-TOCOPHEROL ACETATE; PUNICA GRANATUM WHOLE; Allantoin; Panthenol; DIPOTASSIUM GLUCOSE-6-PHOSPHATE

Dr. Oberon Diaper Rash Baby Cream